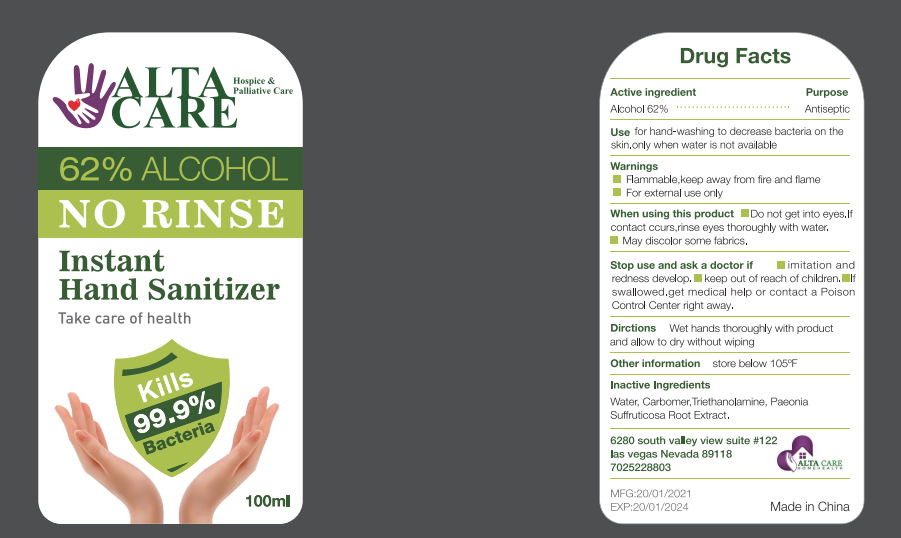 DRUG LABEL: Hand Sanitizer
NDC: 81309-004 | Form: GEL
Manufacturer: LYW BIOTECH CO LIMITED GUANGZHOU
Category: otc | Type: HUMAN OTC DRUG LABEL
Date: 20210220

ACTIVE INGREDIENTS: ALCOHOL 62 mL/100 mL
INACTIVE INGREDIENTS: TROLAMINE 0.4 mL/100 mL; CARBOMER 940 0.4 mL/100 mL; WATER 36 mL/100 mL; PAEONIA SUFFRUTICOSA ROOT 0.2 mL/100 mL

Hand Sanitizer